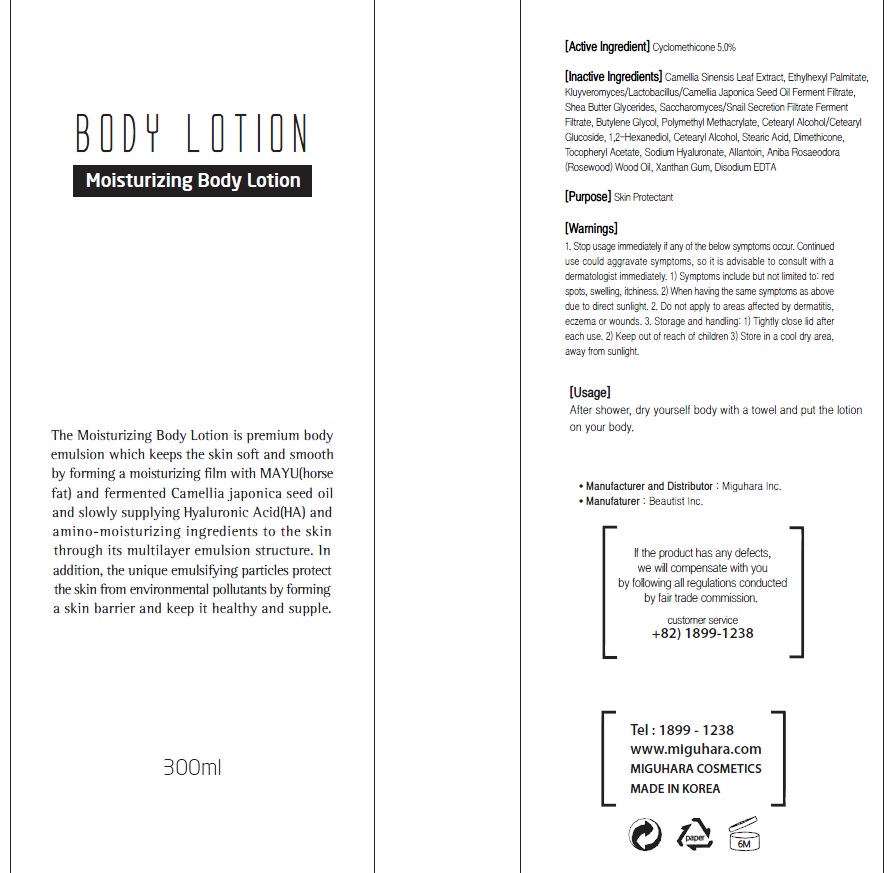 DRUG LABEL: Moisturizing Body
NDC: 70380-270 | Form: LOTION
Manufacturer: MIGUHARA
Category: otc | Type: HUMAN OTC DRUG LABEL
Date: 20160223

ACTIVE INGREDIENTS: Glycerin 15 g/300 mL
INACTIVE INGREDIENTS: GREEN TEA LEAF; Ethylhexyl Palmitate

ACTIVE INGREDIENT

Active Ingredient: Glycerin 5.0%

INACTIVE INGREDIENT

Inactive Ingredients: Camellia Sinensis Leaf Extract, Ethylhexyl Palmitate, Kluyveromyces/Lactobacillus/Camellia Japonica Seed Oil Ferment Filtrate, Shea Butter Glycerides, Saccharomyces/Snail Secretion Filtrate Ferment Filtrate, Butylene Glycol, Polymethyl Methacrylate, Cetearyl Alcohol/Cetearyl Glucoside, 1,2-Hexanediol, Cetearyl Alcohol, Stearic Acid, Dimethicone, Tocopheryl Acetate, Sodium Hyaluronate, Allantoin, Aniba Rosaeodora (Rosewood) Wood Oil, Xanthan Gum, Disodium EDTA

PURPOSE

Purpose: Skin Protectant

WARNINGS

1. Stop usage immediately if any of the below symptoms occur. Continued use could aggravate symptoms, so it is advisable to consult with a dermatologist immediately. 1) Symptoms include but not limited to: red spots, swelling, itchiness. 2) When having the same symptoms as above due to direct sunlight. 2. Do not apply to areas affected by dermatitis, eczema or wounds. 3. Storage and handling: 1) Tightly close lid after each use. 2 Keep out of reach of children 3) Store in a cool dry area, away from sunlight

KEEP OUT OF REACH OF CHILDREN

Usage

Usage: After shower, dry yourself body with a towel and put the lotion on your body.

Usage

Usage: After shower, dry yourself body with a towel and put the lotion on your body.